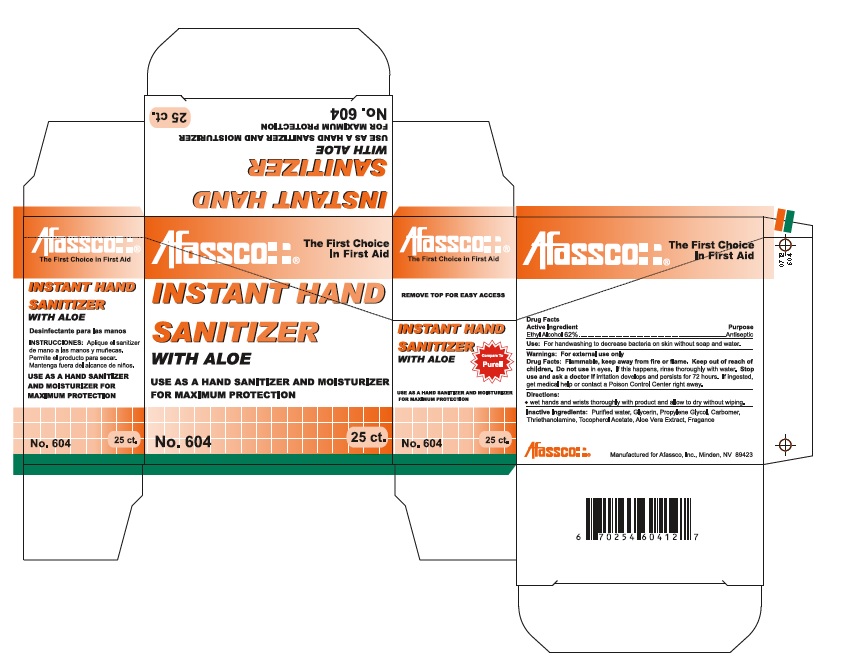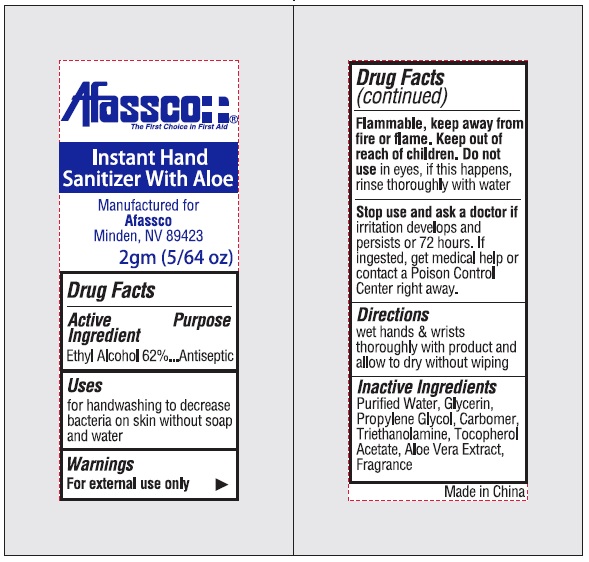 DRUG LABEL: Afassco Instant Hand Sanitizer
NDC: 51532-4604 | Form: GEL
Manufacturer: Afassco Inc.
Category: otc | Type: HUMAN OTC DRUG LABEL
Date: 20190116

ACTIVE INGREDIENTS: ALCOHOL 1.24 g/2 g
INACTIVE INGREDIENTS: WATER; GLYCERIN; PROPYLENE GLYCOL; CARBOXYPOLYMETHYLENE; TROLAMINE; .ALPHA.-TOCOPHEROL ACETATE; ALOE VERA LEAF

Afassco Hand Sanitizer

Drug Facts

Active Ingredient

Ethyl Alcohol 62%

Purpose .....Antiseptic

INDICATIONS AND USAGE

Use: For handwashing to decrease bacteria on skin without soap and water

Warnings: For external use only

OTHER SAFETY INFORMATION

Drug Facts: Flammable, keep away from fire or flame.

Keep out of reach of children.

Do not use in eyes, if this happens, rinse thoroughly with water.

Stop use and ask a doctor if irritation develops and persists or 72 hours. If

ingested, get medical help or contact a Poison Control Center right away.

Directions:

■ wet hands and wrists thoroughly with product and allow to dry without wiping.

INACTIVE INGREDIENT

Inactive Ingredients: Purified water, Glycerin, Propylene Glycol, Carbomer, Triethanolamine,

Tocopherol Acetate, Aloe Vera Extract, Fragrance

Principal Display Panel

Afassco¦ ¦® The First Choice

In First Aid

INSTANT HAND

SANITIZER

WITH ALOE

USE AS A HAND SANITIZER AND MOISTURIZER

FOR MAXIMUM PROTECTION

No. 604 25 ct.

Afassco¦ ¦®

The First Choice in First Aid

REMOVE TOP FOR EASY ACCESS

INSTANT HAND

SANITIZER

WITH ALOE

Compare to

Purell

USE AS A HAND SANITIZER AND MOISTURIZER

FOR MAXIMUM PROTECTION

No. 604 25 ct.

Afassco¦ ¦®

The First Choice in First Aid

INSTANT HAND

SANITIZER

WITH ALOE

Desinfectante para las manos

INSTRUCCIONES: Aplique el sanitizer

de mano a las manos y munecas.

Permite el producto para secar.

Mantenga fuera del alcante de ninos.

USE AS A HAND SANITIZER AND MOISTURIZER

FOR MAXIMUM PROTECTION

No. 604 25 ct.

INSTANT HAND

SANITIZER

WITH ALOE

USE AS A HAND SANITIZER AND MOISTURIZER

FOR MAXIMUM PROTECTION

No. 604 25 ct.

Afassco¦ ¦® The First Choice

In First Aid

Afassco¦ ¦® Manufactured for Afassco, Inc., Minden, NV 89423

6 70254 60412 7

↓Inner Packet↓

Instant hand Sanitizer by Afassco, Inc.

res